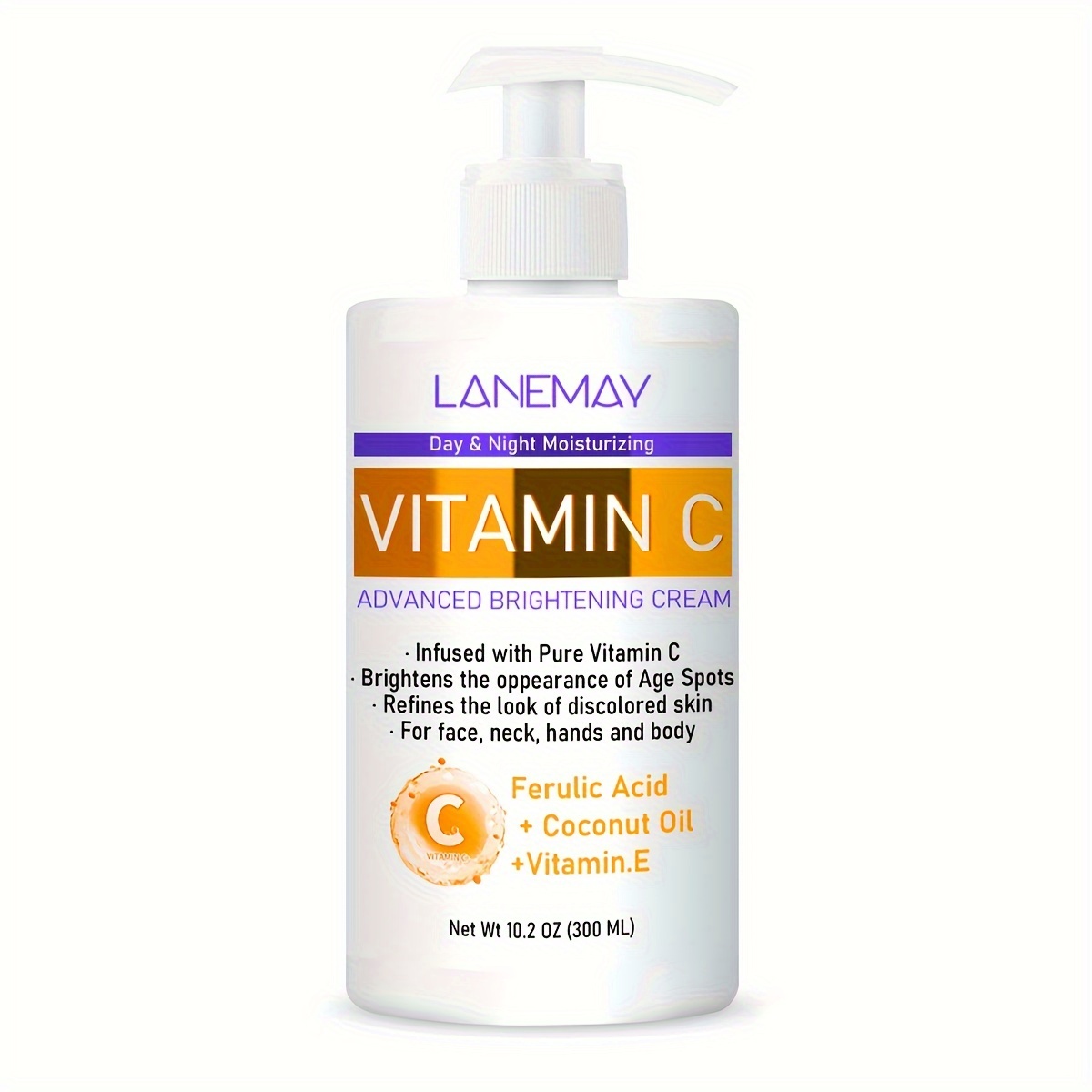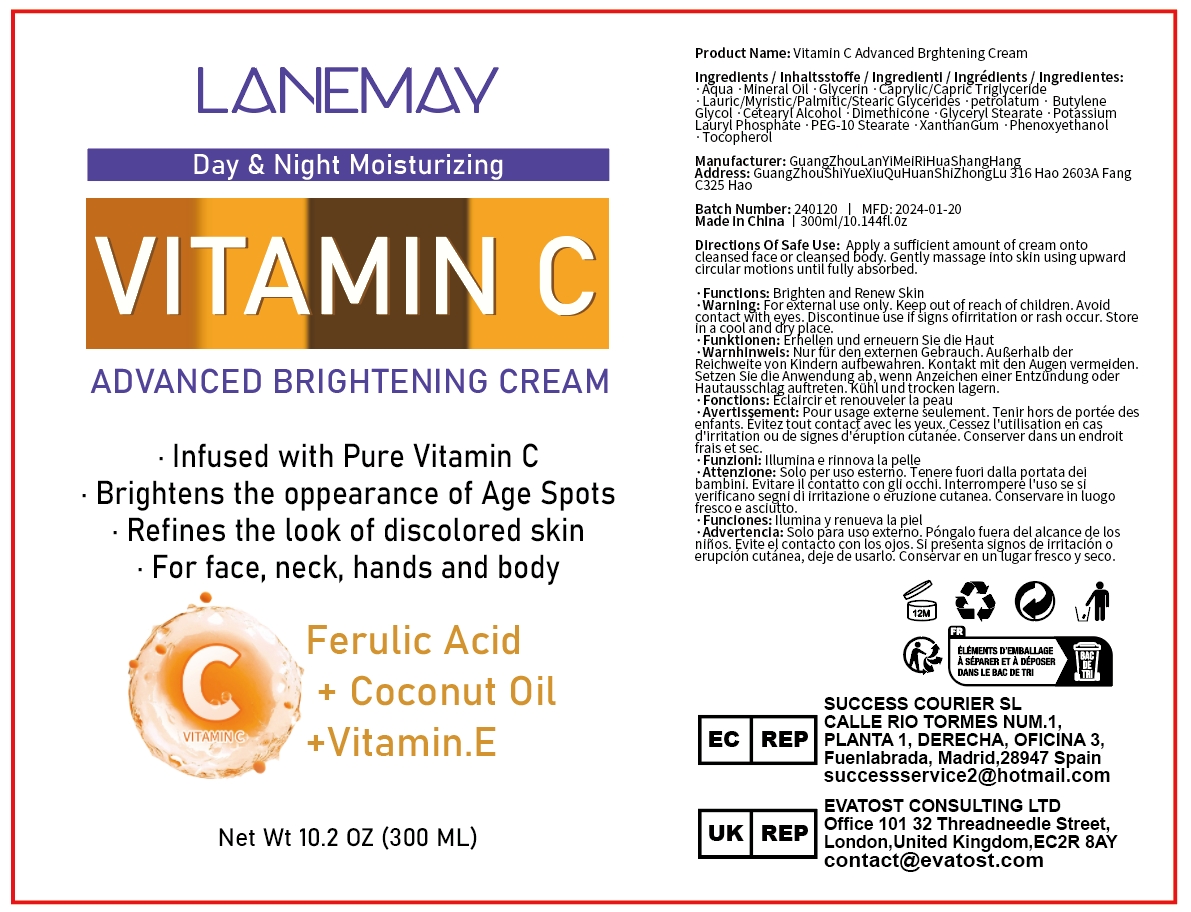 DRUG LABEL: Vitamin C Advanced Brightening Cream
NDC: 84025-033 | Form: CREAM
Manufacturer: Guangzhou Yanxi Biotechnology Co., Ltd
Category: otc | Type: HUMAN OTC DRUG LABEL
Date: 20240407

ACTIVE INGREDIENTS: GLYCERIN 3 mg/100 mL; MINERAL OIL 5 mg/100 mL
INACTIVE INGREDIENTS: WATER

DOSAGE AND ADMINISTRATION

use for body

INACTIVE INGREDIENT

Aqua

INDICATIONS AND USAGE

Apply a sufficient amount of cream onto cleansed face or cleansed body.

Keep out of reach of children.

PURPOSE

Brighten and Renew Skin

WARNINGS

For external use only.